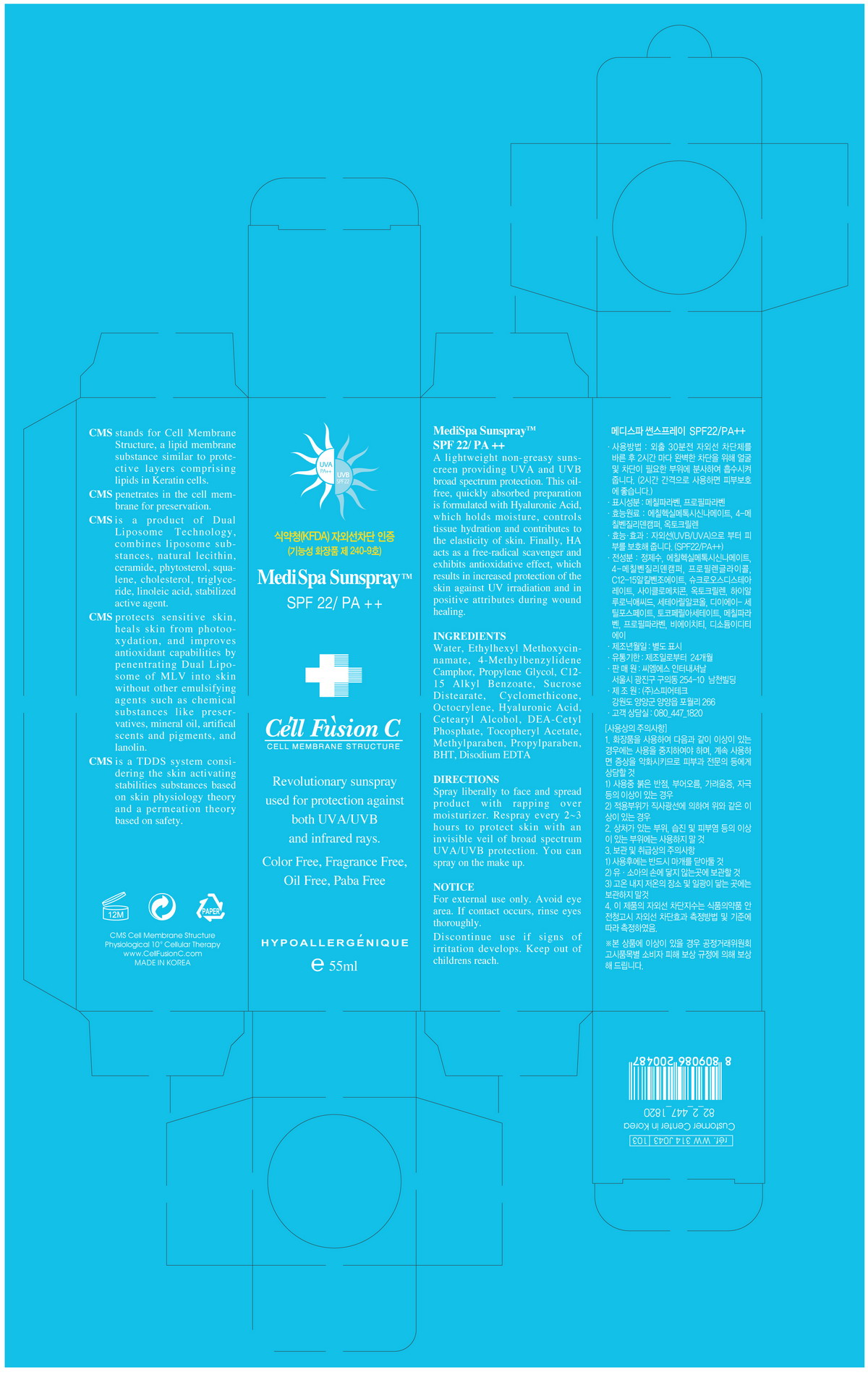 DRUG LABEL: MediSpa SunSpray
NDC: 52554-2001 | Form: SPRAY
Manufacturer: Universal Cosmetic Co., Ltd
Category: otc | Type: HUMAN OTC DRUG LABEL
Date: 20100806

ACTIVE INGREDIENTS: OCTINOXATE 0.075 mL/1 mL; ENZACAMENE 0.05 mL/1 mL; OCTOCRYLENE 0.01 mL/1 mL

Drug Facts

ACTIVE INGREDIENT

Active Ingredients: Ethylhexyl Methoxycinnamate, 4-Methylbenzylidene camphor, Octocrylene

Uses
■ Helps prevent sunburn
■ Provides high protection from sunburn
■ Helps keep moisturize
■ Can be sprayed on powdered face
Warning
For external use only
When using this product
■ Avoid eye area. If contact occurs, rinse eyes thoroughly
■ Discontinue use if signs of irritation develops
Keep out of reach of the children
Direction
■ Spray a proper quantity over the whole face, before finishing skincare.
Other Information
■ store between 20-25 °C (68-77 °F)
■ avoid freezing and excessive heat above 40 °C (104 °F)
■ close cap after use.